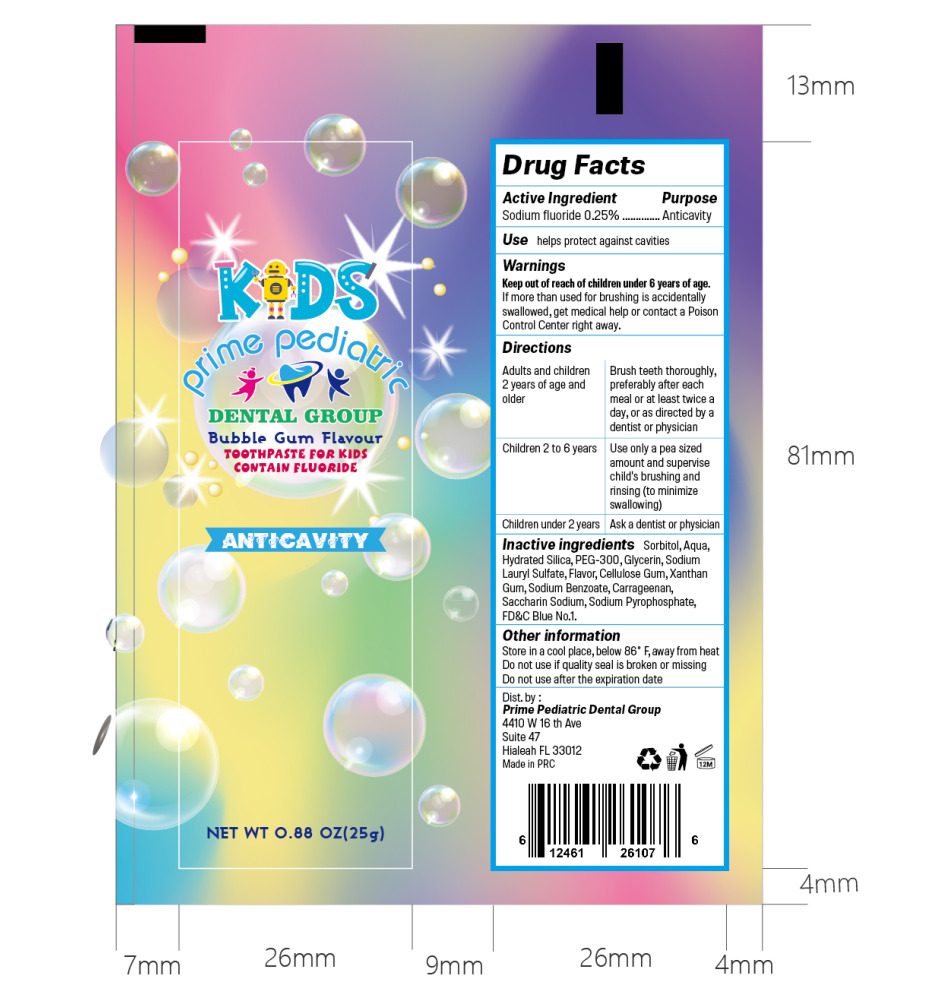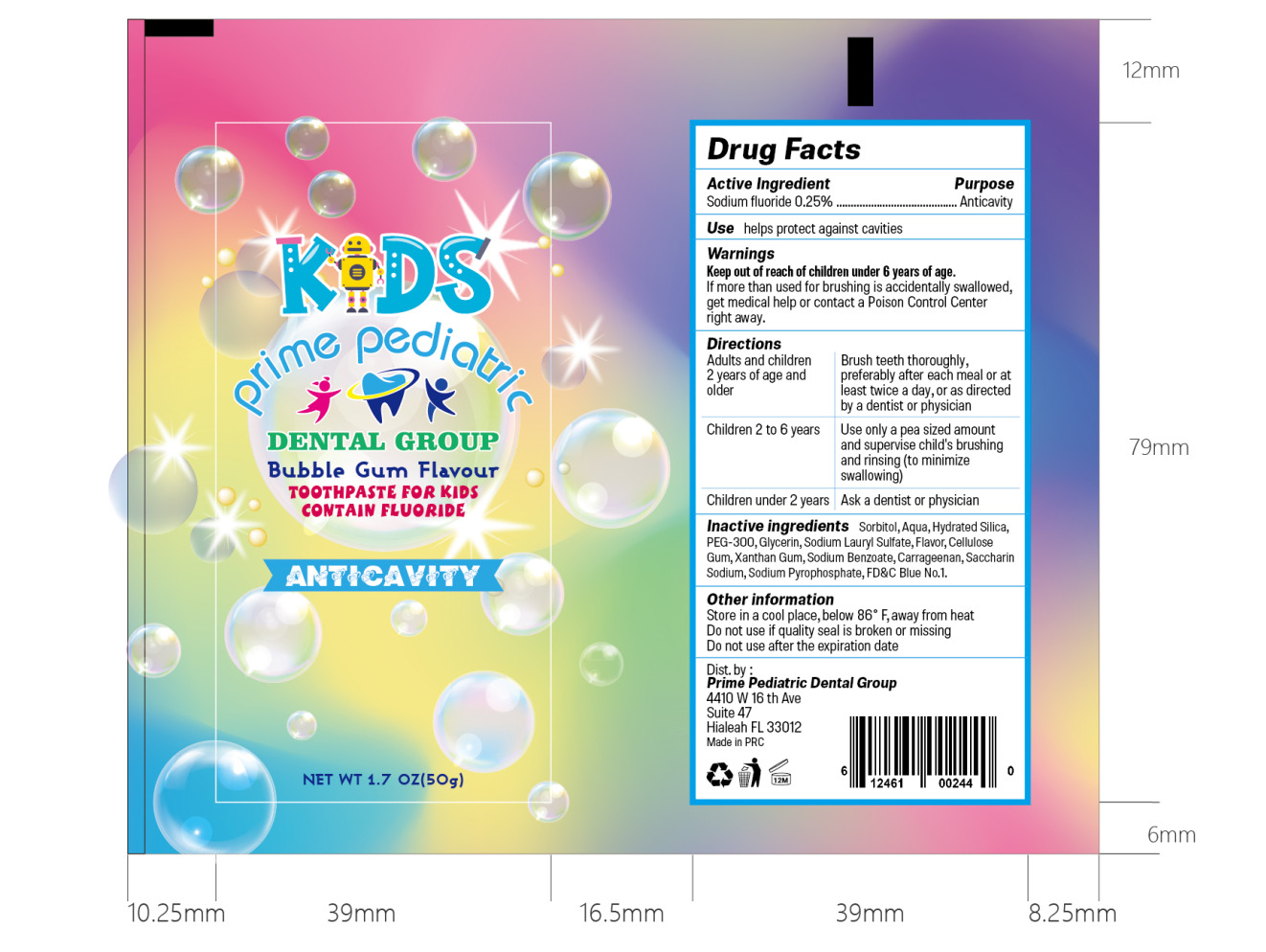 DRUG LABEL: Bubble Gum Flavor For Kids 25g 50g
NDC: 85215-001 | Form: OINTMENT
Manufacturer: WORLD DENTISTS ASSOCIATION AMERICA LIMITED
Category: otc | Type: HUMAN OTC DRUG LABEL
Date: 20250516

ACTIVE INGREDIENTS: SODIUM FLUORIDE 0.25 g/100 g
INACTIVE INGREDIENTS: SODIUM SACCHARIN; SODIUM PYROPHOSPHATE; SORBITOL; AQUA; SILICA; POLYETHYLENE GLYCOL 14000; GLYCERIN; SODIUM LAURYL SULFATE; SCHISANDRA CHINENSIS FRUIT; XANTHAN GUM; SODIUM BENZOATE; CARRAGEENAN

85215-001
Bubble Gum Flavor Toothpaste For Kids 25g&50g

Active Ingredient(s)

Sodium Fluoride 0.25%

Purpose

Anticavity

Use

Use helps protect against cavities

Warnings

Keep out of reach of children under 6 years of age.
If more than used for brushing is accidentally
swallowed, get medical help or contact a Poison
Control Center right away.

Do not use

Do not apply on open skin wounds

WHEN USING

In case of contact with eyes, rinse eyes thoroughly with water.

STOP USE

Minimize swallowing

Keep out of reach of children under 6 years of age.

Directions

Adults and children 2 years of age and older
Brush teeth thoroughly,preferably after each meal or at least twice a day, or as directed by a dentist or physician
Children 2 to 6 years
Use only a pea sized amount and supervise child's brushing and rinsing (to minimize swallowing)
Children under 2years
Ask a dentist or physician

Other information

Store in a cool place, below 86° F, away from heat
Do not use if quality seal is broken or missing
Do not use after the expiration date

Inactive ingredients

Inactive ingredients Sorbitol, Aqua, Hydrated Silica,
PEG-300, Glycerin, Sodium Lauryl Sulfate, Flavor, Cellulose
Gum, Xanthan Gum, Sodium Benzoate, Carrageenan, Saccharin
Sodium, Sodium Pyrophosphate, FD&C Blue No.1.